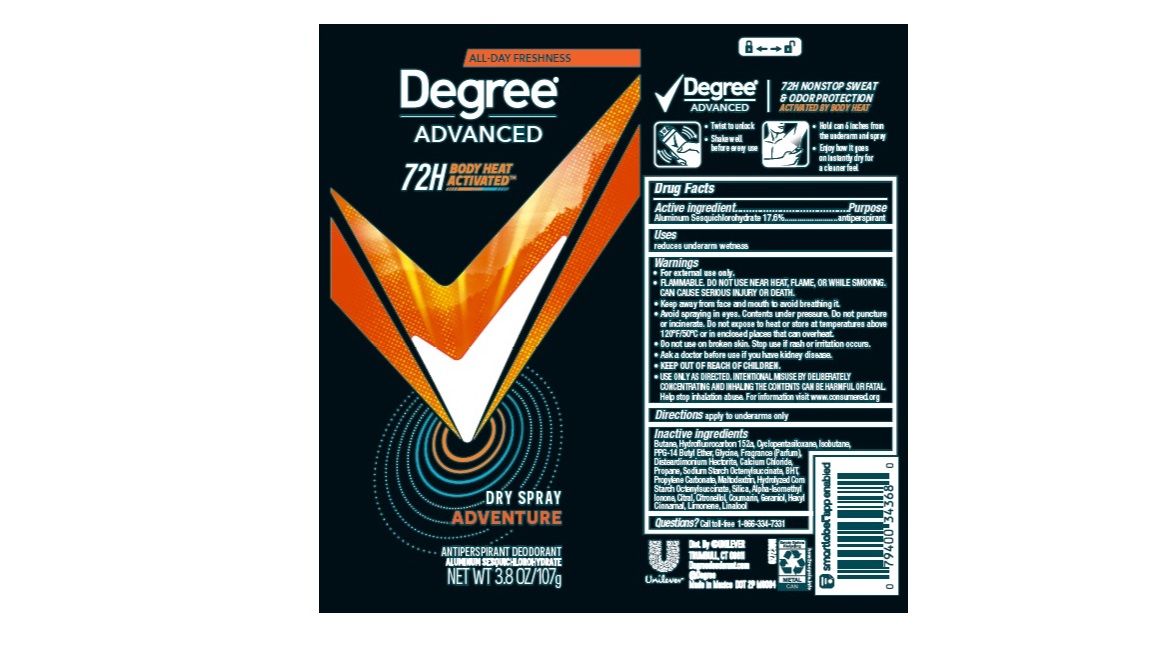 DRUG LABEL: Degree
NDC: 64942-2258 | Form: AEROSOL, SPRAY
Manufacturer: Conopco, Inc. d/b/a Unilever
Category: otc | Type: HUMAN OTC DRUG LABEL
Date: 20240205

ACTIVE INGREDIENTS: ALUMINUM SESQUICHLOROHYDRATE 17.6 g/100 g
INACTIVE INGREDIENTS: ISOMETHYL-.ALPHA.-IONONE; .BETA.-CITRONELLOL, (R)-; LINALOOL, (+/-)-; SILICON DIOXIDE; MALTODEXTRIN; PROPYLENE CARBONATE; GLYCINE; LIMONENE, (+)-; ISOBUTANE; CITRAL; BUTANE; 1,1-DIFLUOROETHANE; CYCLOMETHICONE 5; PPG-14 BUTYL ETHER; DISTEARDIMONIUM HECTORITE; CALCIUM CHLORIDE; PROPANE; BUTYLATED HYDROXYTOLUENE; .ALPHA.-HEXYLCINNAMALDEHYDE; COUMARIN; GERANIOL

Degree Advanced Adventure Dry Spray 72H Antiperspirant Deodorant

Drug Facts

Active ingredient

Aluminum Sesquichlorohydrate (17.6%)

Purpose

antiperspirant

Uses

reduces underarm wetness

Directions

For underarms use only

Inactive ingredients

Butane, Hydrofluorocarbon 152a, Cyclopentasiloxane, Isobutane, PPG-14 Butyl Ether, Glycine, Fragrance (Parfum), Disteardimonium Hectorite, Calcium Chloride, Propane, Sodium Starch Octenylsuccinate, BHT, Propylene Carbonate, Maltodextrin, Hydrolyzed Corn Starch Octenylsuccinate, Silica, Alpha-Isomethyl Ionone, Citral, Citronellol, Coumarin, Geraniol, Hexyl Cinnamal, Limonene, Linalool

Questions?

Call toll-free 1-866-334-7331